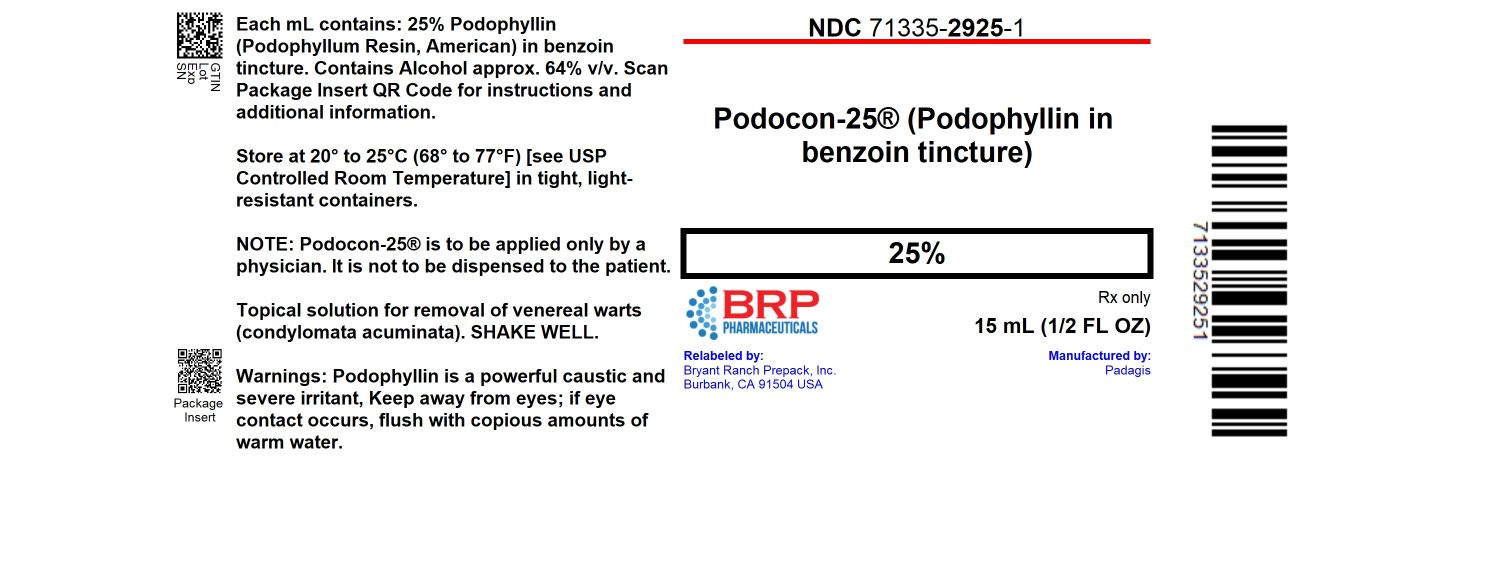 DRUG LABEL: Podocon 25
NDC: 71335-2925 | Form: TINCTURE
Manufacturer: Bryant Ranch Prepack
Category: prescription | Type: HUMAN PRESCRIPTION DRUG LABEL
Date: 20251021

ACTIVE INGREDIENTS: PODOPHYLLUM RESIN 1 mg/4 mL
INACTIVE INGREDIENTS: STYRAX BENZOIN RESIN; ALCOHOL

Podocon-25®
(25% Podophyllin in benzoin tincture)

DESCRIPTION:

Podocon-25® is composed of Podophyllin (Podophyllum Resin, American) 25% in Benzoin Tincture. Podophyllum Resin is the powdered mixture of resins removed from the May apple or Mandrake (Podophyllum peltatum Linne’), a perennial plant of northern and middle United States(1). The podophyllin resin used in this product is exclusively the American podophyllin (rather than the Indian resin). American podophyllin typically has a reduced level of podophyllotoxin (see below).

CLINICAL PHARMACOLOGY:

Podophyllin is a cytotoxic agent that has been used topically in the treatment of genital warts. It arrests mitosis in metaphase, an effect it shares with other cytotoxic agents such as the vinca alkaloids(2). The active agent is podophyllotoxin, whose concentration varies with the type of podophyllin used; the American source normally containing one-fourth the amount of podophyllotoxin as the Indian source(3).

NOTE: PODOCON-25® IS TO BE APPLIED ONLY BY A PHYSICIAN. IT IS NOT TO BE DISPENSED TO THE PATIENT.

INDICATIONS:

Podocon-25® (25% podophyllin in benzoin tincture) is indicated for the removal of soft genital (venereal) warts (condylomata acuminata)(4).

CONTRAINDICATIONS:

Podocon-25® is contraindicated in diabetics, patients using steroids or with poor blood circulation. Podocon-25® should not be used on bleeding warts, moles, birthmarks or unusual warts with hair growing from them. It is recommended that Podocon-25® not be used during pregnancy (see Pregnancy warning below).

WARNINGS:

Podophyllin is a powerful caustic and severe irritant. Keep away from the eyes; if eye contact occurs, flush with copious amounts of warm water and consult physician or poison control center immediately for advice.

PRECAUTIONS:

Do not use Podocon-25® if wart or surrounding tissue is inflamed or irritated. Do not use on bleeding warts, moles, birthmarks or unusual warts with hair growing from them.

ADVERSE REACTIONS:

The use of topical podophyllin has been known to result in paresthesia, polyneuritis, paralytic ileus, pyrexia, leukopenia, thrombocytopenia, coma and death(5).

Pregnancy:

There have been reports of complications associated with the topical use of podophyllin on condylomata of pregnant patients including birth defects, fetal death and stillbirth(6). In the absence of controlled safety studies, podophyllin remains contraindicated for use on pregnant patients.

Nursing Mothers:

It is not known whether podophyllin is excreted in human milk following topical application. In the absence of controlled safety studies, podophyllin remains contraindicated for use on nursing patients.

DOSAGE AND ADMINISTRATION:

PODOCON-25® IS TO BE APPLIED ONLY BY A PHYSICIAN. IT IS NOT TO BE DISPENSED TO THE PATIENT. SHAKE WELL. Thoroughly cleanse affected area. Use supplied applicator to apply Podocon-25® sparingly to lesion. Avoid contact with healthy tissue. Allow to dry thoroughly. Only intact (no bleeding) lesions should be treated. As podophyllin is a powerful caustic and severe irritant, it is recommended the first application of Podocon-25® be left in contact for only a short time (30-40 minutes) to determine patient’s sensitivity. To avoid systemic absorption, time of contact should be minimum time necessary to produce the desired result (1 to 4 hours, depending on condition of lesion and of patient), the physician developing his/her own experience and technique. Large areas or numerous warts should not be treated at once.

After treatment time has elapsed, remove dried Podocon-25® thoroughly with alcohol or soap and water.

HOW SUPPLIED:

Podocon-25® is available in 15-mL bottles with tapered tip applicator attached inside cap.

NDC: 71335-2925-1: 15 mL in a BOTTLE, WITH APPLICATOR

Store at 20° to 25°C (68° to 77°F) [see USP Controlled Room Temperature] in tight, light-resistant containers.

Repackaged/Relabeled by:
Bryant Ranch Prepack, Inc.
Burbank, CA 91504

PACKAGE LABEL

Podophyllum Resin 25% Tincture #15